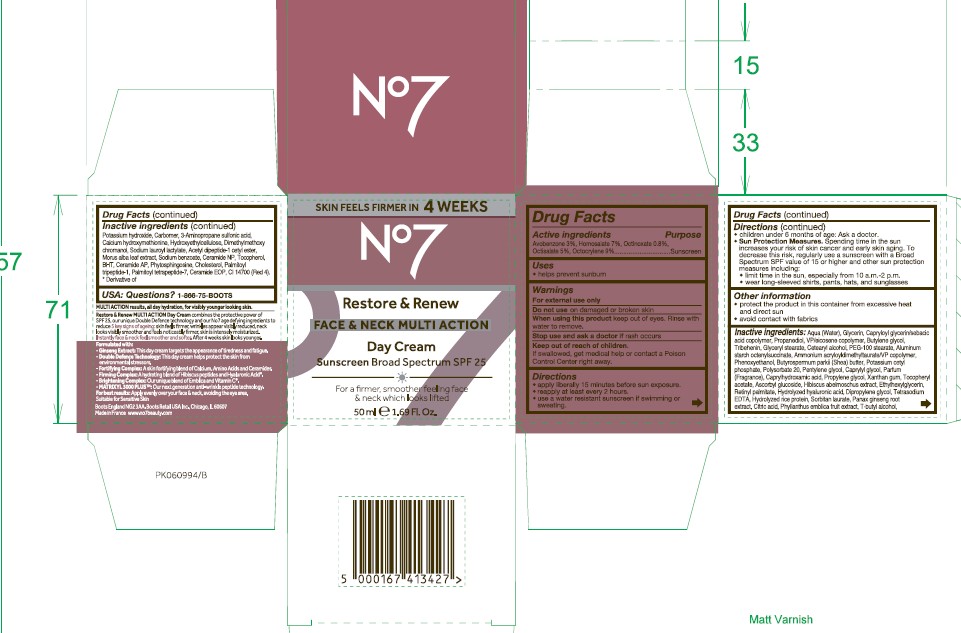 DRUG LABEL: No7 Restore and Renew Multi Action Day Cream Sunscreen Broad Spectrum SPF 25
NDC: 61589-9103 | Form: CREAM
Manufacturer: BCM Cosmetique SAS
Category: otc | Type: HUMAN OTC DRUG LABEL
Date: 20251205

ACTIVE INGREDIENTS: AVOBENZONE 3 g/50 mL; OCTOCRYLENE 9 g/50 mL; OCTISALATE 5 g/50 mL; ETHYLHEXYL METHOXYCINNAMATE 0.8 g/50 mL; HOMOSALATE 7 g/50 mL
INACTIVE INGREDIENTS: CALCIUM HYDROXYMETHIONINE; CI 14700; POLYSORBATE 20; POTASSIUM HYDROXIDE; MORUS ALBA LEAF; CERAMIDE 3; SODIUM BENZOATE; PHYTOSPHINGOSINE; CERAMIDE 6 II; CHOLESTEROL; ETHYLHEXYLGLYCERIN; TOCOPHEROL; CERAMIDE 1; PALMITOYL TRIPEPTIDE-1; PALMITOYL TETRAPEPTIDE-7; ASIAN GINSENG; ACETYL TYROSYLARGININE CETYL ESTER; ABELMOSCHUS MOSCHATUS WHOLE; HYALURONATE SODIUM; SORBITAN MONOLAURATE; WATER; GLYCERIN; ALUMINUM STARCH OCTENYLSUCCINATE; TRIBEHENIN; AMMONIUM ACRYLOYLDIMETHYLTAURATE/VP COPOLYMER; PHENOXYETHANOL; SHEA BUTTER; POTASSIUM CETYL PHOSPHATE; BUTYLENE GLYCOL; PROPYLENE GLYCOL; SODIUM LAUROYL LACTYLATE; PHYLLANTHUS EMBLICA FRUIT; XANTHAN GUM; HYDROXYETHYL CELLULOSE (100 MPA.S AT 2%); VITAMIN A PALMITATE; TERT-BUTYL ALCOHOL; GLYCERYL STEARATE SE; CAPRYLOYL GLYCERIN/SEBACIC ACID COPOLYMER (2000 MPA.S); PENTYLENE GLYCOL; CAPRYLHYDROXAMIC ACID; ASCORBYL GLUCOSIDE; 3-AMINOPROPANE SULFONIC ACID; BHT; HYDROLYZED RICE PROTEIN (ENZYMATIC; 2000 MW); CITRIC ACID; VINYLPYRROLIDONE/EICOSENE COPOLYMER; DIMETHYLMETHOXY CHROMANOL; CARBOMER; PEG-100 STEARATE; CAPRYLYL GLYCOL; PROPANEDIOL; ALPHA-TOCOPHEROL ACETATE; TETRASODIUM EDTA; CETEARYL ALCOHOL

No7 Restore and Renew Face and Neck Multi Action Day Cream Sunscreen Broad Spectrum SPF 25

Carton Active Ingredients Section

Active ingredients

Avobenzone 3%

Homosalate 7%

Octinoxate 0.8%

Octisalate 5%

Octocrylene 9%

Uses

helps prevent sunburn

Warnings

For external use only

Do not use on damaged or broken skin

When using this product keep out of eyes. Rinse with water to remove.

Warnings

For external use only

Do not use on damaged or broken skin

When using this product keep out of eyes. Rinse with water to remove.

Ask a doctor

Stop use and ask a doctor if rash occurs

Keep out of reach of children

If swallowed, get medical help or contact a Poison Control Center right away.

Directions

apply liberally 15 minutes before sun exposure.

reapply at least every 2 hours.

use a water resistant sunscreen if swimming or sweating.

children under 6 months of age: Ask a doctor.

Sun Protection Measures. Spending time in the sun increases your risk of skin cancer and early skin aging.

To decrease this risk, regularly use a sunscreen with a Broad Spectrum SPF value of 15 or higher and other sun protection measures including:

Limit time in the sun, especially from 10 a.m - 2 p.m.

wear long-sleeved shirts,pants,hats and sunglasses.

Directions

apply liberally 15 minutes before sun exposure.

reapply at least every 2 hours.

use a water resistant sunscreen if swimming or sweating.

children under 6 months of age: Ask a doctor.

Sun Protection Measures. Spending time in the sun increases your risk of skin cancer and early skin aging.

To decrease this risk, regularly use a sunscreen with a Broad Spectrum SPF value of 15 or higher and other sun protection measures including:

Limit time in the sun, especially from 10 a.m - 2 p.m.

wear long-sleeved shirts,pants,hats and sunglasses.

Storage

Other information

protect the product in this container from excessive heat and direct sun

avoid contact with fabrics

Inactive ingredients

Aqua (Water), Glycerin, Capryloyl glycerin/sebacic acid copolymer, Propanediol, VP/eicosene copolymer, Butylene glycol, Tribehenin, Glyceryl stearate, Cetearyl alcohol, PEG-100 stearate, Aluminum starch octenylsuccinate, Ammonium acryloydimethyltaurate/VP copolymer, Phenoxyethanol, Butyrospermum parkii (Shea) butter, Potassium cetyl phosphate, Polysorbate 20, Pentylene glycol, Caprylyl glycol, Parfum (Fragrance), Caprylhydroxamic acid, Propylene glycol, Xanthan gum, Tocopheryl acetate, Ascorbyl glucoside, Hibiscus abelmoschus extract, Ethylhexylglycerin, Retinyl palmitate, Hydrolyzed hyaluronic acid, Dipropylene glycol, Tetrasodium EDTA, Hydrolyzed hyaluronic acid, Dipropylene glycol, Hydrolyzed rice protein, Sorbitan laurate, Panax ginseng root extract, Citric acid, Phyllanthus emblica fruit extract, T-butyl alcohol, Potassium hydroxide, Carbomer, 3-aminopropane sulfonic acid, Calcium hydroxymethionine, Hydroxyethylcellulose, Dimethylmethoxy chromanol, Sodium lauroyl lactylate, Acetyl dipeptide-1 cetyl ester, Morus alba leaf extract, Sodium benzoate, Ceramide NP, Tocopherol, BHT, Ceramide AP, Phytosphingsine, Cholesterol, Palmitoyl tripeptide-1, Palmitoyl tetrapeptide-7, Ceramide EOP, CI 14700 (Red 4).

Description

No7 Restore & Renew FACE & NECK MULTI ACTION Anti-Ageing Skincare System

5 key age defying results for FACE & NECK:

Noticeably firmer feeling skin

Wrinkles appear visbly reduced

A more even looking skin tone

Neck looks visibly smoother and feels noticeably firmer

Younger looking skin

50 ml e 1.69 Fl.Oz.

Day Cream:

MULTI ACTION results, all day hydration for visibly younger looking skin.

Combining the protective power of SPF 30, our unique Double Defence technology and our No7 age defying ingredients.

The perfect partner to your No7 Restore & Renew MULTI ACTION serum, this day cream works to visibly reduce the appearance of 5 key signs of ageing: skin feels firmer, wrinkles appear visibly reduced, neck looks visibly smoother and feels noticeably firmer, skin is intensely moisturized.

PATIENT COUNSELING INFORMATION

USA: Questions? 1-866-75-BOOTS

Made in the UK

The Boots Company PLC

Nottingham England NG2 3AA

Dist. in the USA by Boots Retail USA Inc. New York NY 10005

www.no7beauty.com